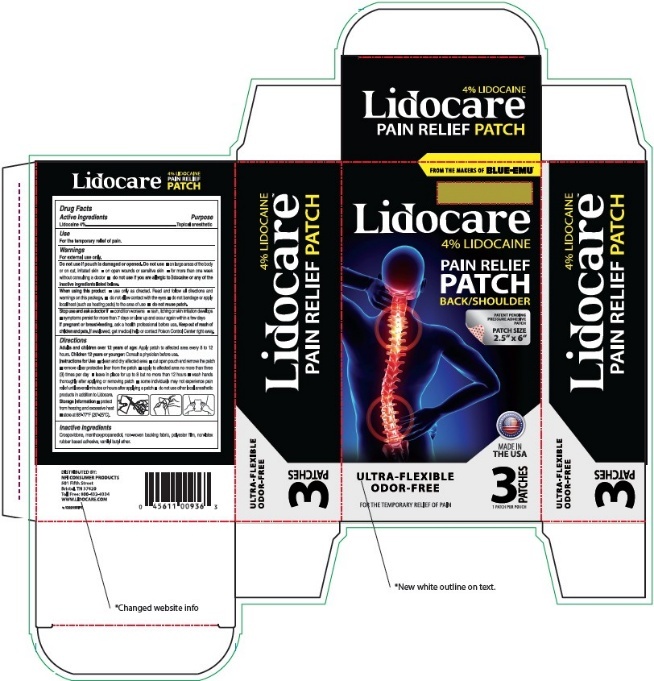 DRUG LABEL: Lidocare
NDC: 69993-400 | Form: PATCH
Manufacturer: Kingsway Pharmaceuticals dba NFI, LLC
Category: otc | Type: HUMAN OTC DRUG LABEL
Date: 20250106

ACTIVE INGREDIENTS: LIDOCAINE 4 g/1 1
INACTIVE INGREDIENTS: CROSPOVIDONE, UNSPECIFIED; 3-(L-MENTHOXY)-2-METHYLPROPANE-1,2-DIOL; VANILLYL BUTYL ETHER

Lidocaine Back / Shoulder Patch

Active Ingredients

Lidocaine 4%

Purpose

Topical anesthetic

Use

For the temporary relief of pain.

Warnings

For external use only.

Do not use if pouch is damaged or opened. Do not use

- on large areas of the body or on cut, irritated skin
- on open wounds or sensitive skin
- for more than one week without consulting a doctor
- do not use if you are allergic to lidocaine or any of the inactive ingredients listed below.

When using this product

- use only as directed. Read and follow all directions and warnings on this package.
- do not allow contact with the eyes
- do not bandage or apply local heat (such as heating pads) to the area of use
- do not reuse patch.

Stop use and ask doctor if

- condition worsens
- rash, itching or skin irritation develops
- symptoms persist for more than 7 days or clear up and occur again within a few days

If pregnant or breast feeding,

ask a health professional before use.

Keep out of reach of children and pets.

If swallowed, get medical help or contact Poison Control Center right away.

Directions

Adults and children over 12 years of age: Apply patch to affected area every 8 to 12 hours.
Children 12 years or younger: Consult a physician before use.

Instructions for Use

- clean and dry affected area
- cut open pouch and remove the patch
- remove clear protective liner from the patch
- apply to affected area no more than three (3) times per day
- leave in place for up to 8 but no more than 12 hours
- wash hands thoroughly after applying or removing patch
- some individuals may not experience pain relief until several minutes or hours after applying a patch
- do not use other local anesthetic products in addition to Lidocare.

Storage Information

- protect from freezing or excessive heat
- store at 68°-77°F (20°-25°C).

Inactive Ingredients

Crospovidone, menthoxypropanediol, non-woven backing fabric, polyester film, non-latex rubber based adhesive, vanillyl butyl ether.

DISTRIBUTED BY:
NFI CONSUMER PRODUCTS
501 Fifth Street
Bristol, TN 37620
TOLL FREE: 800-432-9334
WWW.LIDOCARE.COM

PRINCIPAL DISPLAY PANEL – 3 Patch Carton Label

FROM THE MAKERS OF BLUE-EMU®
Lidocare™
4% LIDOCAINE
PAIN RELIEF
PATCH
BACK/SHOULDER
PATENT PENDING
PRESSURE ADHESIVE
PATCH
PATCH SIZE
2.5” x 6”
MADE IN
THE USA

ULTRA-FLEXIBLE
ODOR-FREE
FOR THE TEMPORARY RELIEF OF PAIN
3 PATCHES
1 PATCH PER POUCH